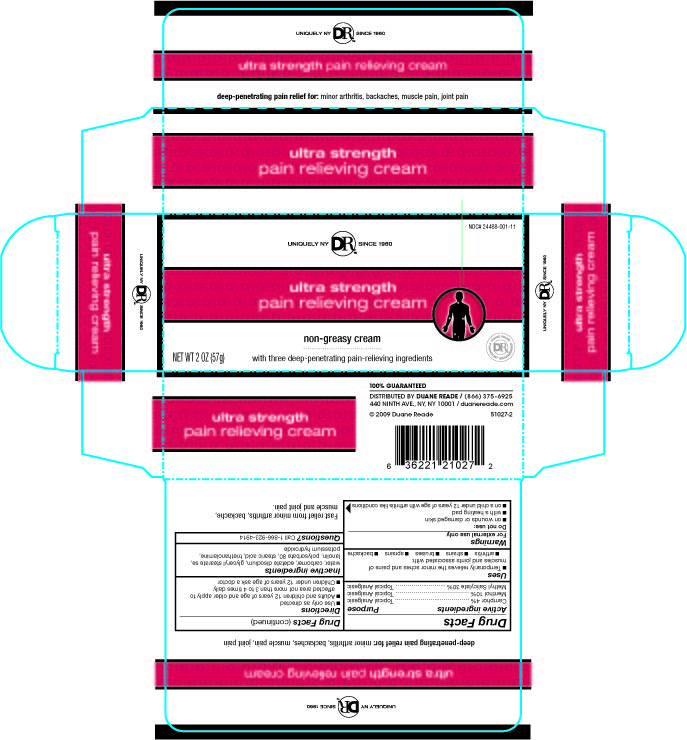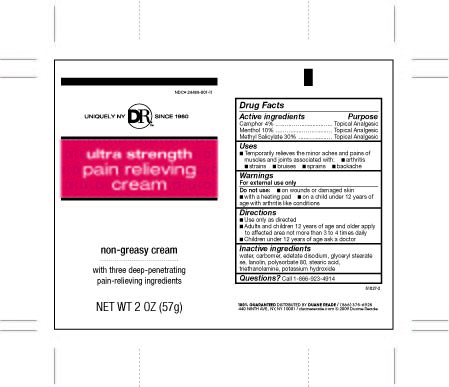 DRUG LABEL: Pain Relieving 
NDC: 24488-001 | Form: CREAM
Manufacturer: Creation's Garden Natural Products, Inc
Category: otc | Type: HUMAN OTC DRUG LABEL
Date: 20100331

ACTIVE INGREDIENTS: CAMPHOR (SYNTHETIC) 2.28 g/57 g; Menthol 5.7 g/57 g; Methyl Salicylate 9 g/57 g
INACTIVE INGREDIENTS: Water; Carbomer Homopolymer Type C; Edetate Disodium; Glyceryl Monostearate ; Lanolin; Polysorbate 80; Stearic Acid; Trolamine; Potassium Hydroxide

Drug Facts

ACTIVE INGREDIENT

Camphor 4% .……..…….............….. Topical Analgesic
Menthol 10% ...……......……….....… Topical Analgesic
Methyl Salicylate 30% .......….......… Topical Analgesic

Uses

■ Temporarily relieves the minor aches and pains of
muscles and joints associated with: ■ arthritis
■ strains ■ bruises ■ sprains ■ backache

Warnings

For external use only

Do not use: ■ on wounds or damaged skin
■ with a heating pad ■ on a child under 12 years of
age with arthritis like conditions

Directions

■ Use only as directed
■ Adults and children 12 years of age and older apply
to affected area not more than 3 to 4 times daily
■ Children under 12 years of age ask a doctor

Inactive ingredients

water, carbomer, disodium edta, glyceryl stearate se,
lanolin, polysorbate 80, stearic acid, triethanolamine,
potassium hydroxide

Questions?

Questions? Call 1-866-923-4914